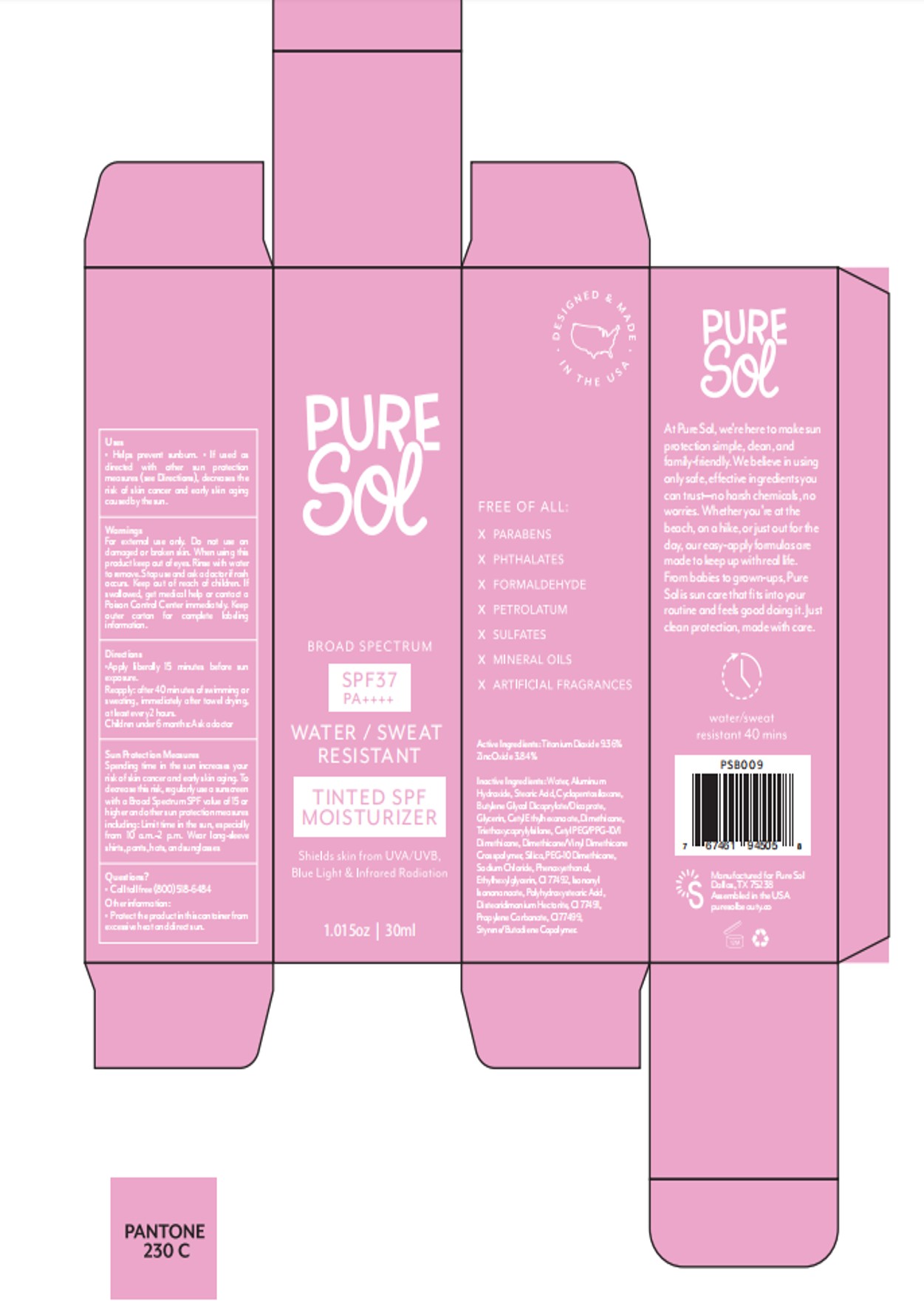 DRUG LABEL: PURE SOL SPF 37 Tinted Moisturizer
NDC: 84090-004 | Form: LIQUID
Manufacturer: Brand 2022b LLC
Category: otc | Type: HUMAN OTC DRUG LABEL
Date: 20251004

ACTIVE INGREDIENTS: TITANIUM DIOXIDE 9.36 g/100 mL; ZINC OXIDE 3.84 g/100 mL
INACTIVE INGREDIENTS: CI 77492; METHACRYLATE/METHOXY PEG-10 MALEATE/STYRENE COPOLYMER; GLYCERIN; BUTYLENE GLYCOL DICAPRYLATE/DICAPRATE; POLYHYDROXYSTEARIC ACID STEARATE; STEARIC ACID; CI 77491; CETYL PEG/PPG-10/1 DIMETHICONE (HLB 5); WATER; CETYL PEG/PPG-10/1 DIMETHICONE (HLB 2); DISTEARDIMONIUM HECTORITE; CYCLOPENTASILOXANE; CETYL ETHYLHEXANOATE; DIMETHICONE; TRIETHOXYCAPRYLYLSILANE; ETHYLHEXYLGLYCERIN; SILICA; SODIUM CHLORIDE; DIMETHICONE/VINYL DIMETHICONE CROSSPOLYMER (SOFT PARTICLE); POLYHYDROXYSTEARIC ACID (2300 MW); PROPYLENE CARBONATE; CI 77499; PEG-10 DIMETHICONE (600 CST); PHENOXYETHANOL; ALUMINUM HYDROXIDE; ISONONYL ISONONANOATE

84090-004-01.PURE SOL SPF 37 Tinted Moisturizer- Liquid-30ml

ACTIVE INGREDIENT

Zinc Oxide 3.84%
TITANIUM DIOXIDE 9.36%

PURPOSE

WATER /SWEATRESISTANT
TINTED SPFMOISTURIZER
Shields skin from UVA/UVBBlue Light & Infrared Rodiotion

Keep out of reach of children.lf swallowed, get medical help or contacta Poison Control Center right away

WARNINGS

For external use only Do not use on damaged or broken skin.
When using this product: keep out of eyes, Rinse with water to remove.
Stop use and ask a doctor if rash occurs.
Keep out of reach of children.lf swallowed, get medical help or contacta Poison Control Center right away
Flammable. Do not spray near heat sparks, sources of ignition, or flames

DOSAGE AND ADMINISTRATION

Apply tiberally 15 minutes before sun exposure.
Reapoly. at least every 2 hours or after 40 minutes of swimming or sweating.

INACTIVE INGREDIENT

WATER
ALUMINUM HYDROXIDE
STEARIC ACID
CYCLOPENTASILOXANE
BUTYLENE GLYCOL DICAPRYLATE/DICAPRATE
GLYCERIN
CETYL ETHYLHEXANOATE
DIMETHICONE
TRIETHOXYCAPRYLYLSILANE
CETYL PEG/PPG-10/1 DIMETHICONE
DIMETHICONE/VINYL DIMETHICONE CROSSPOLYMER
SILICA
PEG-10 DIMETHICONE
SODIUM CHLORIDE
PHENOXYETHANOL
ETHYLHEXYLGLYCERIN
CI 77492
ISONONYL ISONONANOATE
CETYL PEG/PPG-10/1 DIMETHICONE
POLYHYDROXYSTEARIC ACID
TRIETHOXYCAPRYLYLSILANE
DISTEARDIMONIUM HECTORITE
WATER
CI 77491
ISONONYL ISONONANOATE
DISTEARDIMONIUM HECTORITE
PROPYLENE CARBONATE
CI 77499
POLYHYDROXYSTEARIC ACID
STYRENE/BUTADIENE COPOLYMER

INDICATIONS AND USAGE

Apply liberally 15 minutes before sun exposure
Reapply
After 40 minutes of swimming or sweating
Immediately after towel drying
At least every 2 hours
Sun Protection Measures. Spending time in the sun increases your risk of skin cancer and early skin aging. To decrease this risk, regularly use a sunscreen with a broad spectrum SPF of 15 or higher and other sun protection measures including:
Limit time in the sun, especially from 10 a.m. - 2 p.m.